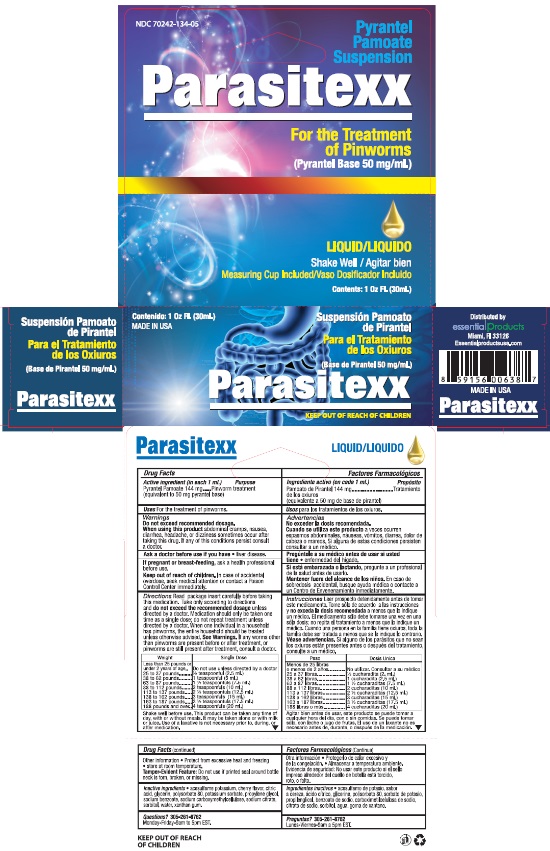 DRUG LABEL: Parasitexx
NDC: 70242-134 | Form: SUSPENSION
Manufacturer: Dannso Corp./d.b.a. Essential Products
Category: otc | Type: HUMAN OTC DRUG LABEL
Date: 20220102

ACTIVE INGREDIENTS: PYRANTEL PAMOATE 144 mg/1 mL
INACTIVE INGREDIENTS: ACESULFAME POTASSIUM; CHERRY; CITRIC ACID ACETATE; POLYSORBATE 80; POTASSIUM SORBATE; PROPYLENE GLYCOL; SODIUM BENZOATE; SODIUM CITRATE; SORBITOL; WATER; XANTHAN GUM

PARASITEXX

Active Ingredient

Active Ingredient (in each 1 ml) Purpose

Active Ingredient (in each 1 ml) | Purpose
PYRANTEL PAMOATE | Pinworm Treatment

Inactive Ingredient

acesulfame potassium, cherry flavor, citric acid, glycerin, polysorbate 80, potassium sorbate, propylene glycol, sodium benzoate, sodium carboxymethylcellulose, sodium citrate, sorbitol, water, xanthan gum.

Dosage

Directions Read package insert careful before taking this medication. Take only according to directions and do not exceed the recommended dosage unless directed by a doctor. Medication should only be taken one time as a single dose; do not repeat treatment unless directed by a doctor. When one individual in a household has pinworms, the entire household should be treated unless otherwise advised. See warnings. If any worms other than pinworms are present before or after treatment, or pinworms are still present after treatment, consult a doctor.

WEIGHTS SINGLE DOSE
Less than 26 pounds or under 2 years of age | Do not use unless directed by a doctor
25 to 37 pounds | ½ teaspoonful (2.5 ml)
38 to 62 pounds | 1 teaspoonful (5 ml)
63 to 87 pounds | 1 ½ teaspoonfuls (7.5 ml)
88 to 112 pounds | 2 teaspoonfuls (10 ml)
113 to 137 pounds | 2 ½ teaspoonfuls (12.5 ml)
138 to 162 pounds | 3 teaspoonfuls (15 ml)
163 to 187 pounds | 3 ½ teaspoonfuls (17.5 ml)
188 pounds and over | 4 teaspoonfuls (20 ml)

Shake well before use. This product can be taken any time of the day, with or without meals. It may be taken alone or with milk or juice. Use of a laxative is not necessary prior to, during, or after medication.

Uses

For the treatment of pinworms.

Warnings

Do not exceed recommended dosage. When using this product abdominal cramps, nausea, diarrhea. Headache, or dizziness sometimes occurs after taking this drug. If this condition persists consult doctor.

Ask a doctor before use if you have liver disease.

PREGNANCY OR BREAST FEEDING

If pregnant or breast-feeding, ask a health professional before use.

INDICATIONS AND USAGE

Uses for the treatment of pinworns

Keep out of reach of children.

In case of accidental overdose, seek medical attention or contact a Poison Control Center immediately.

Other information

Protect from excessive heat and freezing. Store at room temperature.

Tamper-Evident Feature: do not use if printed seal around bottle neck is torn, broken or missing.

Questions? 305-261-8762
Monday – Friday 9am to 5pm EST.